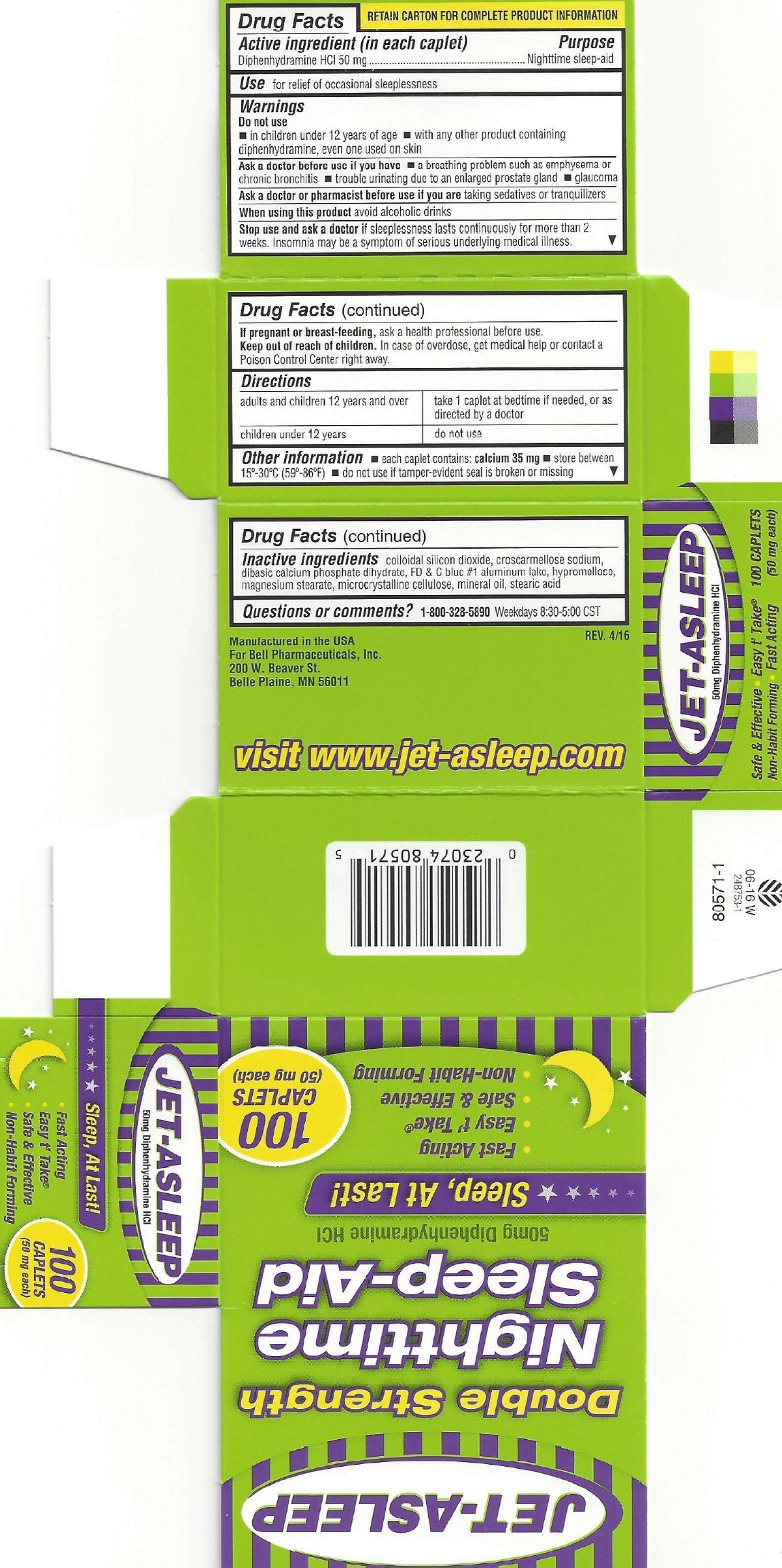 DRUG LABEL: Jet-Asleep Double Strength Night Time Sleep Aid
NDC: 15579-828 | Form: TABLET
Manufacturer: Bell Pharmaceuticals, Inc.
Category: otc | Type: HUMAN OTC DRUG LABEL
Date: 20231215

ACTIVE INGREDIENTS: DIPHENHYDRAMINE HYDROCHLORIDE 50 mg/1 1
INACTIVE INGREDIENTS: SILICON DIOXIDE; CROSCARMELLOSE SODIUM; DIBASIC CALCIUM PHOSPHATE DIHYDRATE; FD&C BLUE NO. 1; MAGNESIUM STEARATE; MICROCRYSTALLINE CELLULOSE; MINERAL OIL; STEARIC ACID

Jet-Asleep Double Strength Night Time Sleep Aid

Active ingredient (in each caplet)

Diphenhydramine HCL 50mg

Purpose

Nighttime sleep-aid

Uses

- for relief of occasional sleeplessness

Warnings

Do not use

- in children under 12 years of age
- with any other product containing diphenhydramine, even one used on skin

Ask a doctor before use if you have

- a breathing problem such as emphysema or chronic bronchitis
- traouble urinating due to a to enlarged prostate gland
- glaucome

Ask a doctor or pharmacist before useif you are

- taking Sedatives or tranquilizers

When using this product

avoid alcoholic drinks

Stop use and ask a doctor

if sleeplessness lasts continuosly for more than 2 weeks. Insomnia may be a symptom of serious underlying medical illness.

If pregnant or breast-feeding,

ask a health professional before use.

Keep out of reach of children.

In case of overdose, get medical help or contact a Poison Control Center right away.

Directions

adults and children 12 years and over | take 1 caplets at bedtime if needed, or as directed by a doctor
children under 12 years | do not ues

Other information

- each caplet contains:calcium 35 mg
- store between 15°-30°C (59°-86°F)
- don not use if tamper-evident seal is broken or missing

Inactive ingredients

colloidal silicon dioxide, croscarmellose sodium, dibasic calcium phosphate dihydrate, FD & C blue #1 aluminum lake, hypromellose, magnesium stearate, microcrystalline cellulose, mineral oil, stearic acid

Questions or comments?

1-800-328-5890 Weekdays 8:30-5:00 CST